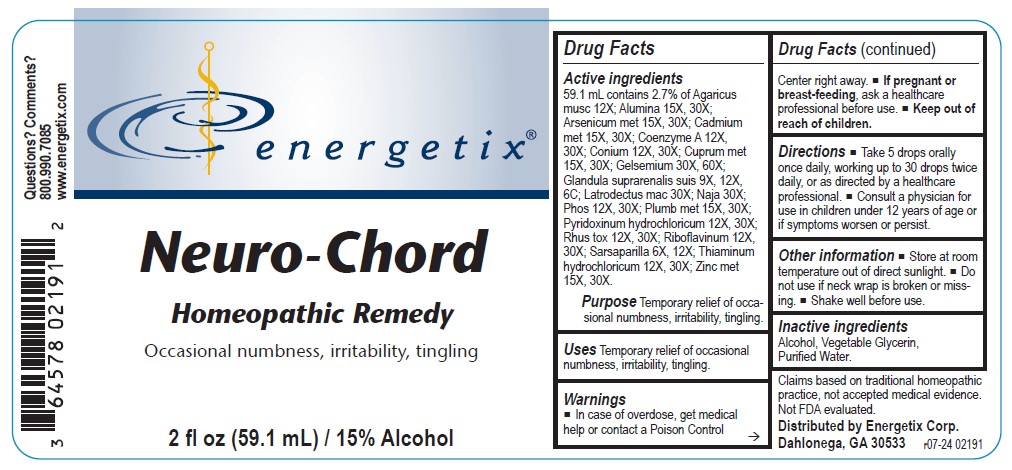 DRUG LABEL: Neuro-Chord
NDC: 64578-0180 | Form: LIQUID
Manufacturer: Energetix Corporation
Category: homeopathic | Type: HUMAN OTC DRUG LABEL
Date: 20251217

ACTIVE INGREDIENTS: GELSEMIUM SEMPERVIRENS ROOT 30 [hp_X]/59.1 mL; SUS SCROFA ADRENAL GLAND 9 [hp_X]/59.1 mL; LATRODECTUS MACTANS 30 [hp_X]/59.1 mL; NAJA NAJA VENOM 30 [hp_X]/59.1 mL; PHOSPHORUS 12 [hp_X]/59.1 mL; LEAD 15 [hp_X]/59.1 mL; PYRIDOXINE HYDROCHLORIDE 12 [hp_X]/59.1 mL; TOXICODENDRON PUBESCENS LEAF 12 [hp_X]/59.1 mL; RIBOFLAVIN 12 [hp_X]/59.1 mL; SARSAPARILLA 6 [hp_X]/59.1 mL; THIAMINE HYDROCHLORIDE 12 [hp_X]/59.1 mL; ZINC 15 [hp_X]/59.1 mL; AMANITA MUSCARIA FRUITING BODY 12 [hp_X]/59.1 mL; ALUMINUM 15 [hp_X]/59.1 mL; ARSENIC 15 [hp_X]/59.1 mL; CADMIUM 15 [hp_X]/59.1 mL; COENZYME A 12 [hp_X]/59.1 mL; CONIUM MACULATUM FLOWERING TOP 12 [hp_X]/59.1 mL; COPPER 15 [hp_X]/59.1 mL
INACTIVE INGREDIENTS: WATER; ALCOHOL; GLYCERIN

Neuro-Chord

ACTIVE INGREDIENT

Active ingredients59.1 mL contains 2.7% of: Agaricus musc 12X; Alumina 15X, 30X; Arsenicum met 15X, 30X; Cadmium met 15X, 30X; Coenzyme A 12X, 30X; Conium 12X, 30X; Cuprum met 15X, 30X; Gelsemium 30X, 60X; Glandula suprarenalis suis 9X, 12X, 6C; Latrodectus mac 30X; Naja 30X; Phos 12X, 30X; Plumbum met 15X, 30X; Pyridoxinum hydrochloricum 12X, 30X; Rhus tox 12X, 30X; Riboflavinum 12X, 30X; Sarsaparilla 6X, 12X; Tarentula cub 30X; Thiaminum hydrochloricum 12X, 30X; Zinc met 15X, 30X.

Claims based on traditional homeopathic practice, not accepted medical evidence. Not FDA evaluated.

INDICATIONS AND USAGE

UsesTemporary relief of ocassional numbness, irritability, tingling.

Warnings

- In case of overdose, get medical help or contact a Poison Control Center right away.
- If pregnant or breast-feeding, ask a healthcare professional before use.

- Keep out of reach of children.

Directions

- Take 5 drops orally once daily, working up to 30 drops twice daily, or as directed by a healthcare professional.
- Consult a physician for use in children under 12 years of age or if symptoms worsen or persist.

Other information

- Store at room temperature out of direct sunlight.
- Do not use if neck wrap is broken or missing.
- Shake well before use.

Inactive ingredients

Alcohol, Vegetable Glycerin, Purified Water.

QUESTIONS

Distributed by Energetix Corp.

Dahlonega, GA 30533

Questions? Comments?

800.990.7085

www.energetix.com

PACKAGE LABEL

energetix

Neuro-Chord

Homeopathic Remedy

Numbness, irritability, tingling.

2 fl oz (59.1 mL) / 15% Alcohol

PURPOSE

Purpose Temporary relief of occasional numbness, irritability, tingling.